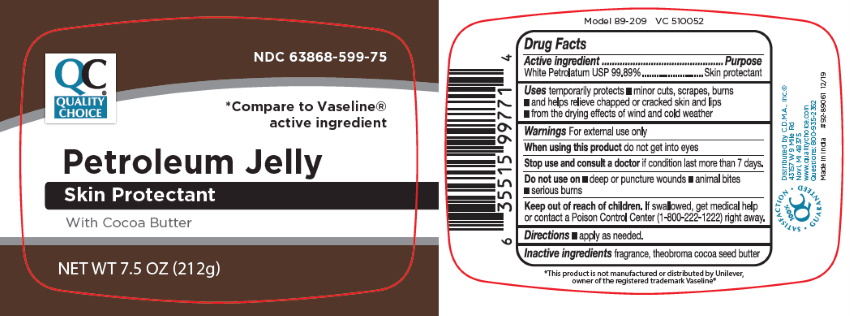 DRUG LABEL: Petroleum with Cocoa
NDC: 63868-599 | Form: JELLY
Manufacturer: QUALITY CHOICE (Chain Drug Marketing Association)
Category: otc | Type: HUMAN OTC DRUG LABEL
Date: 20251117

ACTIVE INGREDIENTS: PETROLATUM 100 g/100 g
INACTIVE INGREDIENTS: COCOA BUTTER

Quality Choice Petrolatum Jelly with Cocoa Butter

Warning

For External Use Only

Active Ingredient

Name Purpose

White Petrolatum 100% USP .............................. Skin Protectant

Inactive Ingredsient

Water

Purpose

Skin Protectant

Keep out of the reach of children

If swallowed, get medical help or contact a Poison Control Center (1-800-222-1222)right away

Uses

Temporarily Protects:

minor cuts, scrapes, burns and helps relieve chapped or cracked skin and lips from the drying effects of wind and cold weather

Dosage

Applied as needed.

Label

NDC:63868-599-75